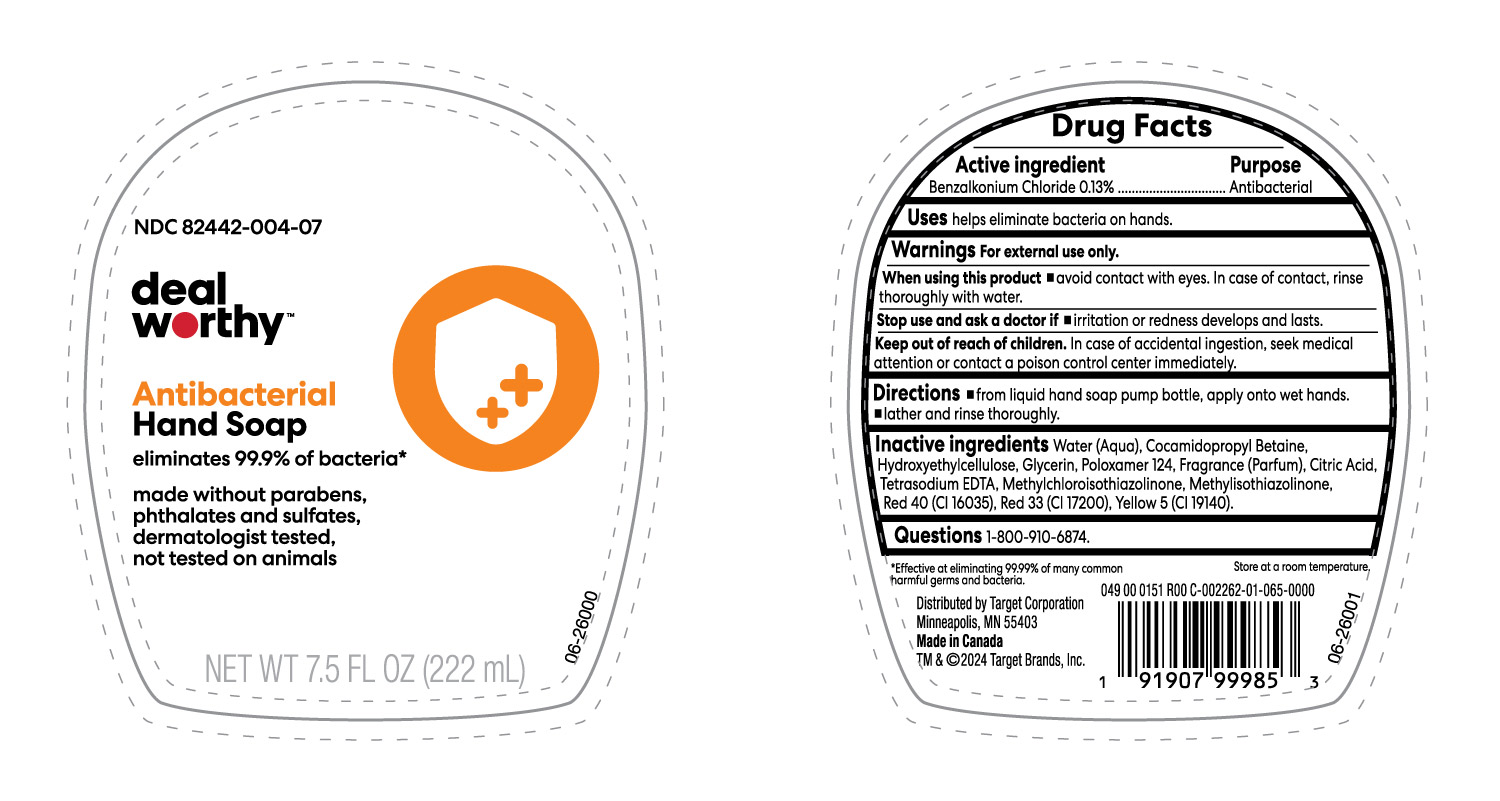 DRUG LABEL: Antibacterial LHS
NDC: 82442-004 | Form: LIQUID
Manufacturer: TARGET CORPORATION INC.
Category: otc | Type: HUMAN OTC DRUG LABEL
Date: 20250206

ACTIVE INGREDIENTS: BENZALKONIUM CHLORIDE 130 mg/100 mL
INACTIVE INGREDIENTS: POLOXAMER 124; METHYLCHLOROISOTHIAZOLINONE; FRAGRANCE CLEAN ORC0600327; METHYLISOTHIAZOLINONE; CITRIC ACID MONOHYDRATE; COCAMIDOPROPYL BETAINE; HYDROXYETHYL CELLULOSE, UNSPECIFIED; D&C RED NO. 33; EDETATE SODIUM; FD&C RED NO. 40; FD&C YELLOW NO. 5; GLYCERIN; WATER

NDC-82442-004-07, Deal Worthy Antibacterial Liq Hand Soap, Target

Active ingredient

Benzalkonium chloride 0.13%

Purpose

Antibacterial

Uses

helps eliminate bacteria on hands.

Warnings

For external use only

When using this product

- Avoid contact with eyes. In case of contact, rinse thoroughly with water.

Stop use and ask a doctor if

- irritation or redness develops and lasts.

Keep out of reach of children.

In case of accidental ingestion, get medical help or contact a Poison Control Center immediately.

Directions

- From Liquid Hand Soap pump bottle, apply onto wet hands.
- Lather and rinse thoroughly.

Inactive ingredients

Water (Aqua), Cocamidopropyl Betaine, Hydroxyethylcellulose, Glycerin, Poloxamer 124, Fragrance (Parfum), Citric Acid, Tetrasodium EDTA, Methylchloroisothiazolinone, Methylisothiazolinone, Red 40 (CI 16035), Red 33 (CI 17200), Yellow 5 (CI 19140).

Questions

1-800-910-6874